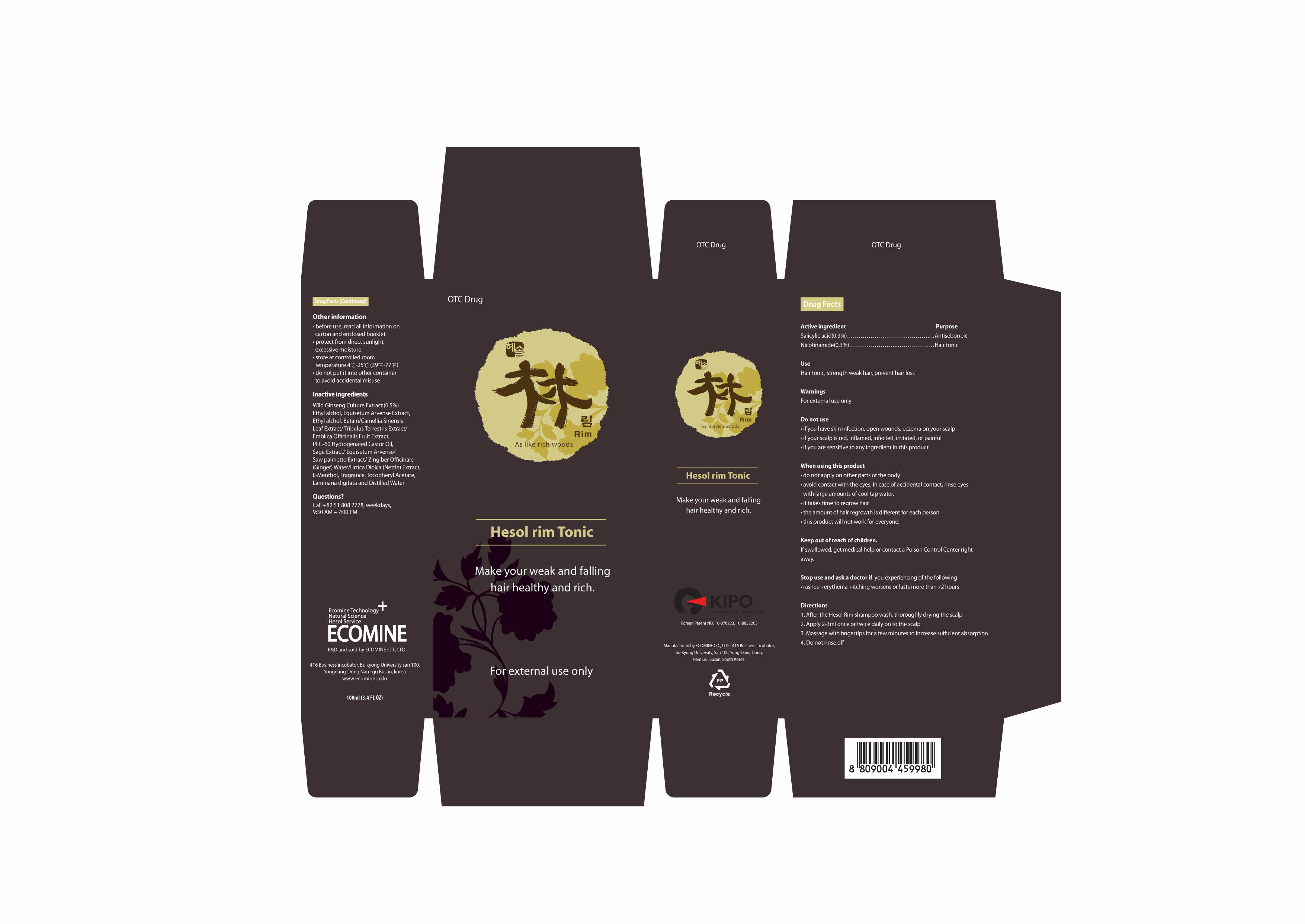 DRUG LABEL: Hesol Rim 
NDC: 51270-112 | Form: LIQUID
Manufacturer: Ecomine Co Ltd
Category: otc | Type: HUMAN OTC DRUG LABEL
Date: 20101001

ACTIVE INGREDIENTS: SALICYLIC ACID 0.3 mL/100 mL; NIACINAMIDE 0.3 mL/100 mL
INACTIVE INGREDIENTS: WATER; ALCOHOL; BETAINE; GREEN TEA LEAF; POLYOXYL 60 HYDROGENATED CASTOR OIL; EQUISETUM ARVENSE TOP; SAW PALMETTO; URTICA DIOICA; MENTHOL; .ALPHA.-TOCOPHEROL ACETATE, D-; GINGER OIL

Ecomine Co Ltd

Drug Facts

Active Ingredient

Salicylic Acid 0.30%
Niacinamide 0.30%

Purpose

Hair Tonic

Keep out of Reach of Children

Stop use and ask a doctor if
- chest pain, rapid heartbeat, faintness, or dizziness occurs
- your hands or feet swell
- scalp irritation or redness occurs
- May be harmful if used when pregnant or breast-feeding.
- Keep out of reach of children if swallowed, get medical help or Poison Control Center right away

Indication & Usage

When using this product
- do not apply on other parts of the body
- avoid contact with the eyes. In case of accidental contact, rinse eyes with large amounts of cool tap water.
- some people have experienced changes in hair color and/or texture
- it takes time to regrow hair
- the amount of hair regrowth is different for each person. This product will not
work for everyone.

Warnings

For external use only
Do not use
- your scalp is red, inflamed, infected, irritated, or painful
- you have no family history of hair loss
- your hair loss is sudden and/or patchy
- your hair loss is associated with childbirth
- you do not know the reason for your hair loss
-you are under 18 years of age. Do not use on babies and children Ask adoctor before use if you have heart disease

Dosage & Administraion

- shake well before using product
- apply an appropriate amount all over scalp every day
- scrub and massage scalp using hands for helping to absorb product Other information
- before use, read all information on carton and enclosed booklet
- store at controlled room temperature 1 to 30℃
- Do not store in hot locations or expose to sunlight

Inactive Ingredient

Water, Alcohol, PEG-60 Hydrogenated Castor Oil, Equisetum Arvense, Saw Palmetto Extract, Menthol, Tocopheryl Acetate

Hesol Rim Tonic

Ecomine Co Ltd
Net WT. 3.4 FL OZ (100mL)